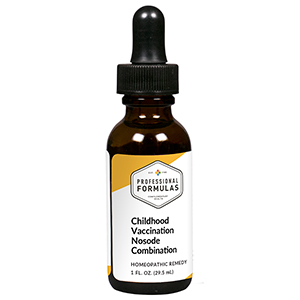 DRUG LABEL: Childhood Vaccination Nosode Combination
NDC: 63083-9409 | Form: LIQUID
Manufacturer: Professional Complementary Health Formulas
Category: homeopathic | Type: HUMAN OTC DRUG LABEL
Date: 20190815

ACTIVE INGREDIENTS: ANTIMONY POTASSIUM TARTRATE 6 [hp_X]/29.5 mL; HAMAMELIS VIRGINIANA ROOT BARK/STEM BARK 6 [hp_X]/29.5 mL; QUININE SULFATE 8 [hp_X]/29.5 mL; SULFUR 8 [hp_X]/29.5 mL; CROTALUS HORRIDUS HORRIDUS VENOM 10 [hp_X]/29.5 mL; MERCURIUS SOLUBILIS 12 [hp_X]/29.5 mL; POLIOVIRUS TYPE 1 ANTIGEN (FORMALDEHYDE INACTIVATED) 12 [hp_X]/29.5 mL; SILICON DIOXIDE 12 [hp_X]/29.5 mL; THUJA OCCIDENTALIS LEAF 12 [hp_X]/29.5 mL; VACCINIA VIRUS STRAIN NEW YORK CITY BOARD OF HEALTH LIVE ANTIGEN 12 [hp_X]/29.5 mL
INACTIVE INGREDIENTS: ALCOHOL; WATER

R409

ACTIVE INGREDIENTS

Antimonium tartaricum 6X
Hamamelis virginiana 6X
Chininum sulphuricum 8X
Sulphur 8X
Crotalus horridus 10X
Mercurius solubilis 12X
Poliomyelitis 12X
Silicea 12X
Thuja occidentalis 12X
Vaccinotoxinum 12X

QUESTIONS

Professional Formulas

PO Box 2034 Lake Oswego, OR 97035

INDICATIONS

For the temporary relief of occasional headache, minor muscle or joint pain, fatigue, nausea or vomiting, diarrhea, or constipation.*

PURPOSE

*Claims based on traditional homeopathic practice, not accepted medical evidence. Not FDA evaluated.

WARNINGS

Persistent symptoms may be a sign of a serious condition. If symptoms persist or are accompanied by a fever, rash, or persistent headache, consult a doctor. Keep out of the reach of children. In case of overdose, get medical help or contact a poison control center right away. If pregnant or breastfeeding, ask a healthcare professional before use.

Keep out of the reach of children.

PREGNANCY OR BREAST FEEDING

If pregnant or breastfeeding, ask a healthcare professional before use.

DIRECTIONS

Place drops under tongue 30 minutes before/after meals. Adults and children 12 years and over: Take 10 to 15 drops once weekly or monthly. If mild symptoms are present, take 10 drops up to 3 times per day. Consult a physician for use in children under 12 years of age.

OTHER INFORMATION

Tamper resistant. If seal is broken, do not use. After opening, close container tightly and store at room temperature away from heat.

INACTIVE INGREDIENTS

40% ethanol, purified water.

LABEL

Est 1985

Professional Formulas

Complementary Health

Childhood Vaccination Nosode Combination

Homeopathic Remedy

1 FL. OZ. (29.5 mL)